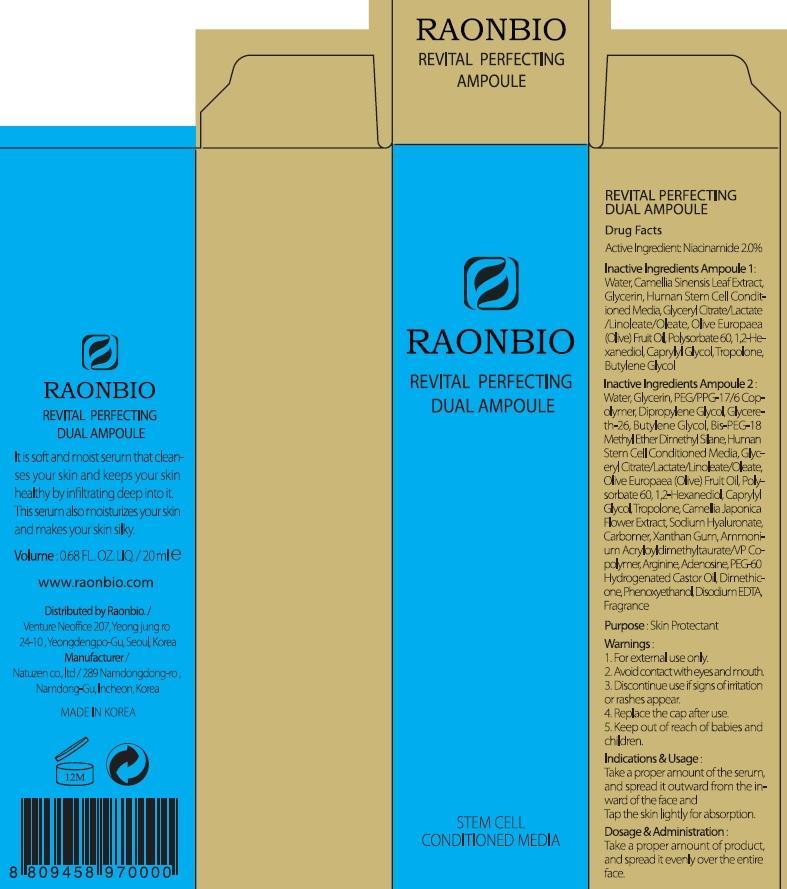 DRUG LABEL: REVITAL PERFECTING DUAL AMPOULE
NDC: 70038-010 | Form: SOLUTION
Manufacturer: RAONBIO CORP
Category: otc | Type: HUMAN OTC DRUG LABEL
Date: 20150820

ACTIVE INGREDIENTS: Niacinamide 0.4 mg/20 mL
INACTIVE INGREDIENTS: Water; Glycerin

ACTIVE INGREDIENT

Active Ingredient: Niacinamide 2.0%

INACTIVE INGREDIENT

Inactive Ingredients Ampoule 1: Water, Camellia Sinensis Leaf Extract, Glycerin, Human Stem Cell Conditioned Media, Glyceryl Citrate/Lactate/Linoleate/Oleate, Olive Europaea (Olive) Fruit Oil, Polysorbate 60, 1,2-Hexanediol, Caprylyl Glycol, Tropolone, Butylene Glycol

Inactive Ingredients Ampoule 2: Water, Glycerin, PEG/PPG-17/6 Copolymer, Dipropylene Glycol, Glycereth-26, Butylene Glycol, Bis-PEG-18 Methyl Ether Dimethyl Silane, Human Stem Cell Conditioned Media, Glyceryl Citrate/Lactate/Linoleate/Oleate, Olive Europaea (Olive) Fruit Oil, Polysorbate 60, 1,2-Hexanediol, Caprylyl Glycol, Tropolone, Camellia Japonica Flower Extract, Sodium Hyaluronate, Carbomer, Xanthan Gum, Ammonium Acryloyldimethyltaurate/VP Copolymer, Arginine, Adenosine, PEG-60 Hydrogenated Castor Oil, Dimethicone, Phenoxyethanol, Disodium EDTA, Fragrance

PURPOSE

Purpose: Skin Protectant

WARNINGS

1. For external use only. 2. Avoid contact with eyes and mouth. 3. Discontinue use if signs of irritation or rashes appear. 4. Replace the cap after use. 5.Keep out of reach of babies and children.

KEEP OUT OF REACH OF CHILDREN

Keep out of reach of babies and children.

INDICATIONS & USAGE

Indications & Usage: Take a proper amount of the serum, and spread it outward from the inward of the face and Tap the skin lightly for absorption.

DOSAGE & ADMINISTRATION

Dosage & Administration: Take a proper amount of product, and spread it evenly over the entire face.